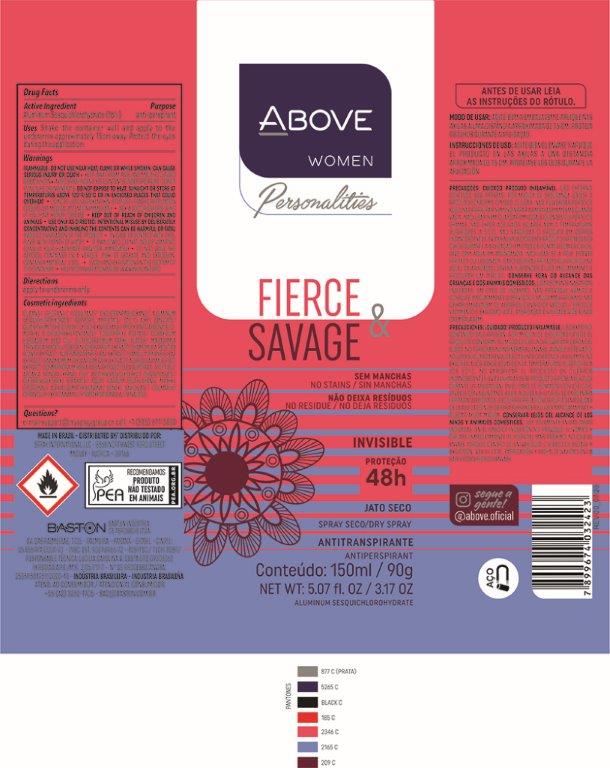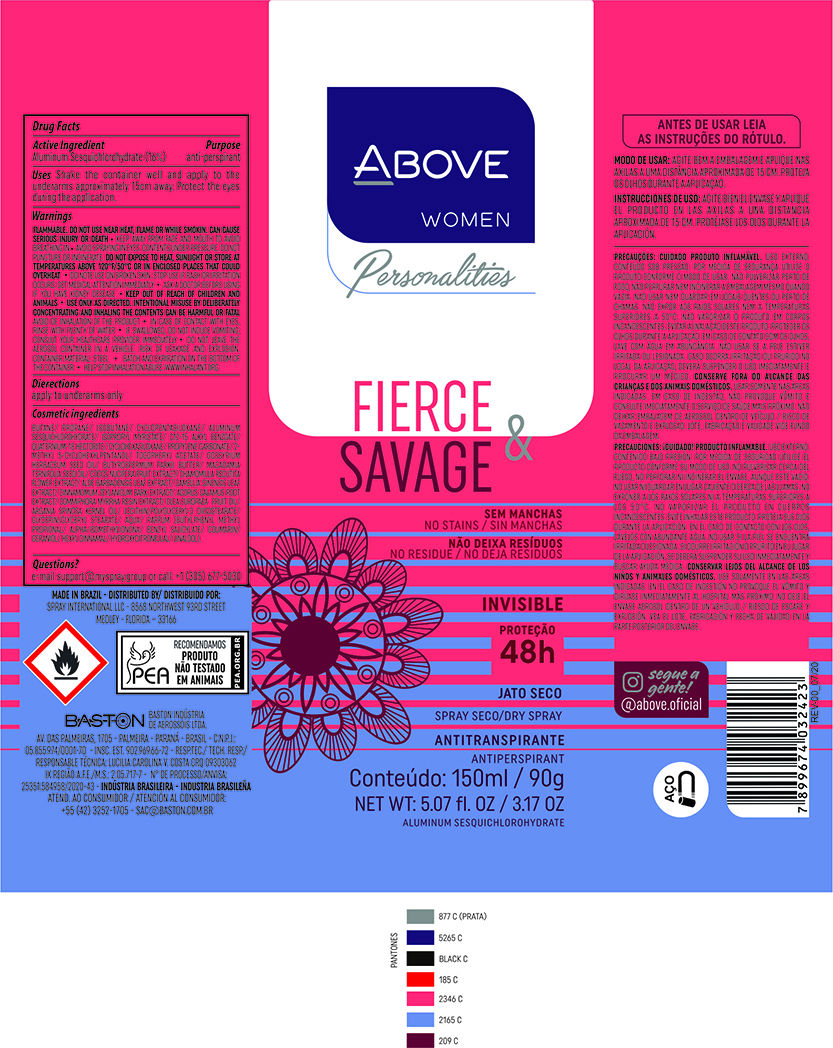 DRUG LABEL: ANTIPERSPIRANT ABOVE PERSONALITIES FIERCE E SAVAGE
NDC: 73306-1124 | Form: AEROSOL, SPRAY
Manufacturer: BASTON INDUSTRIA DE AEROSSÓIS LTDA
Category: otc | Type: HUMAN OTC DRUG LABEL
Date: 20241226

ACTIVE INGREDIENTS: ALUMINUM SESQUICHLOROHYDRATE 16 g/100 g
INACTIVE INGREDIENTS: CHAMOMILE; DISTEARDIMONIUM HECTORITE; ALOE VERA LEAF; .ALPHA.-TOCOPHEROL ACETATE; COCONUT; ALKYL (C12-15) BENZOATE; BUTANE; MYRRH OIL; ISOBUTANE; ARGAN OIL; PROPANE; SHEA BUTTER; DIMETHICONE; GREEN TEA LEAF; GLYCERYL MONOSTEARATE; GLYCERIN; ISOPROPYL MYRISTATE; CYCLOMETHICONE 5; CINNAMON BARK OIL; WATER; 2-METHYL 5-CYCLOHEXYLPENTANOL; MACADAMIA OIL; LECITHIN, SOYBEAN; POLYGLYCERYL-3 DIISOSTEARATE; LEVANT COTTON SEED; ACORUS CALAMUS ROOT; PROPYLENE CARBONATE

ANTIPERSPIRANT ABOVE PERSONALITIES FIERCE E SAVAGE

ACTIVE INGREDIENT

Aluminum sesquichlorohydrate 16%

PURPOSE

Antiperspirant

INDICATIONS AND USAGE

Uses - reduces underarm wetness

DOSAGE AND ADMINISTRATION

Directions -Apply to underarms only

INACTIVE INGREDIENT

BUTANE/PROPANE/ISOBUTANE/CYCLOPENTASILOXANE/ALUMINUM SESQUICHLOROHYDRATE/ISOPROPYL MYRISTATE/C12-15 ALKYL BENZOATE/QUATERNIUM-18 HECTORITE/CYCLOHEXASILOXANE/PROPYLENE CARBONATE/2-METHYL 5-CYCLOHEXYLPENTANOL/TOCOPHERYL ACETATE/GOSSYPIUM HERBACEUM SEED OIL/
BUTYROSPERMUM PARKII BUTTER/MACADAMIA TERNIFOLIA SEED OIL/COCOS NUCIFERA FRUIT EXTRACT/CHAMOMILLA RECUTITA FLOWER EXTRACT/ALOE BARBADENSIS LEAF EXTRACT/CAMELLIA SINENSIS LEAF EXTRACT/CINNAMOMUM ZEYLANICUM BARK EXTRACT/ACORUS CALAMUS ROOT EXTRACT/COMMIPHORA MYRRHA RESIN EXTRACT/OLEA EUROPAEA FRUIT OIL/ARGANIA SPINOSA KERNEL OIL/LECITHIN/POLYGLYCERYL-3 DIISOSTEARATE/GLYCERIN/GLYCERYL STEARATE/AQUA/PARFUM(BUTYLPHENYL METHYL PROPIONAL/ALPHA-ISOMETHYLIONONA/
BENZYL SALICYLATE/COUMARIN/GERANIOL/HEXYL CINNAMAL/HYDROXYCITRONELLAL/LINALOOL).

QUESTIONS

e-mail: sac @baston.com.br or call: +1(305)677-5030

Keep Out Of Reach Of Children

WARNINGS AND PRECAUTIONS

•Flammable until fully dry. Do not use near heat, Flame or while smoking. Can cause serious
injury or deat•Keep away from face and mouth to avoid breathing in•Avoid spraying in
eyes•Contents under pressure•Do not puncture or incinerate•Do not expose to heat or store at
temperatures above 120 ºF/50 ºC or in enclosed places that could overheat•Do not use on
broken skin•Stop use if rash or irritation occurs•Ask a doctor before using if you have kidney
disease•USE ONLY AS DIRECTED•INTENTIONAL MISUSE BY DELIBERATELY
CONCENTRATING AND INHALING THE CONTENTS CAN BE HARMFUL OR
FATAL•Avoid de inhalation of the product.